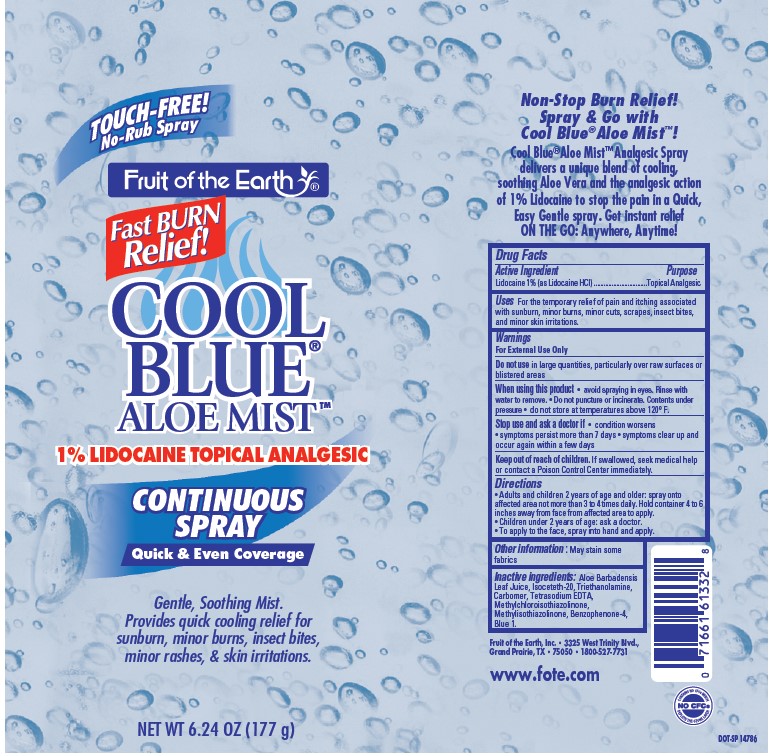 DRUG LABEL: Fruit of the Earth Cool Blue Aloe Mist Continuous
NDC: 62217-095 | Form: SPRAY
Manufacturer: Fruit Of The Earth, Inc.
Category: otc | Type: HUMAN OTC DRUG LABEL
Date: 20241018

ACTIVE INGREDIENTS: LIDOCAINE HYDROCHLORIDE 10 mg/1 g
INACTIVE INGREDIENTS: ALOE VERA LEAF; ISOCETETH-20; TROLAMINE; CARBOMER HOMOPOLYMER TYPE C (ALLYL PENTAERYTHRITOL CROSSLINKED); EDETATE SODIUM; METHYLCHLOROISOTHIAZOLINONE/METHYLISOTHIAZOLINONE MIXTURE; SULISOBENZONE; FD&C BLUE NO. 1; WATER

Fruit of the Earth Cool Blue Aloe Mist Continuous Spray

Active Ingredients

Lidocaine 1% (as Lidocaine HCl)

Purpose

Topical Analgesic

Uses

For the temporary relief of pain and itching associated with sunburn, minor burns, minor cuts, scrapes, insect bites, and minor skin irritations.

Warnings

For External Use Only

Do not use

in large quantities, particularly over raw surfaces or blistered areas

When using this product

- Avoid sprying in eyes. Rinse with water to remove.
- Do not puncture or incinerate. Contents under pressure.
- do not store at temperatures above 120°F.

Stop use and ask a doctor if

- condition worsens
- symptoms persist more than 7 days
- symptoms clear up and occur again within a few days

Keep out of reach of children

If swallowed, seek medical help or contact a Poison Control Center immediately.

Directions

- Adults and children 2 years of age and older; spray onto affected area not more than 3 to 4 times daily. Hold container 4 to 6 inches away from face from affected area to apply
- Children under 2 years of age: ask a doctor.
- To apply to the face, spray into hand and apply.

Other information

May stain some fabrics.

Inactive Ingredients

Aloe Barbadensis Leaf Juice, Isoceteth-20, Triethanolamine, Carbomer, Tetrasodium EDTA, Methylchloroisothiazolinone, Methylisothiazolinone, Benzophenone-4, Blue 1.